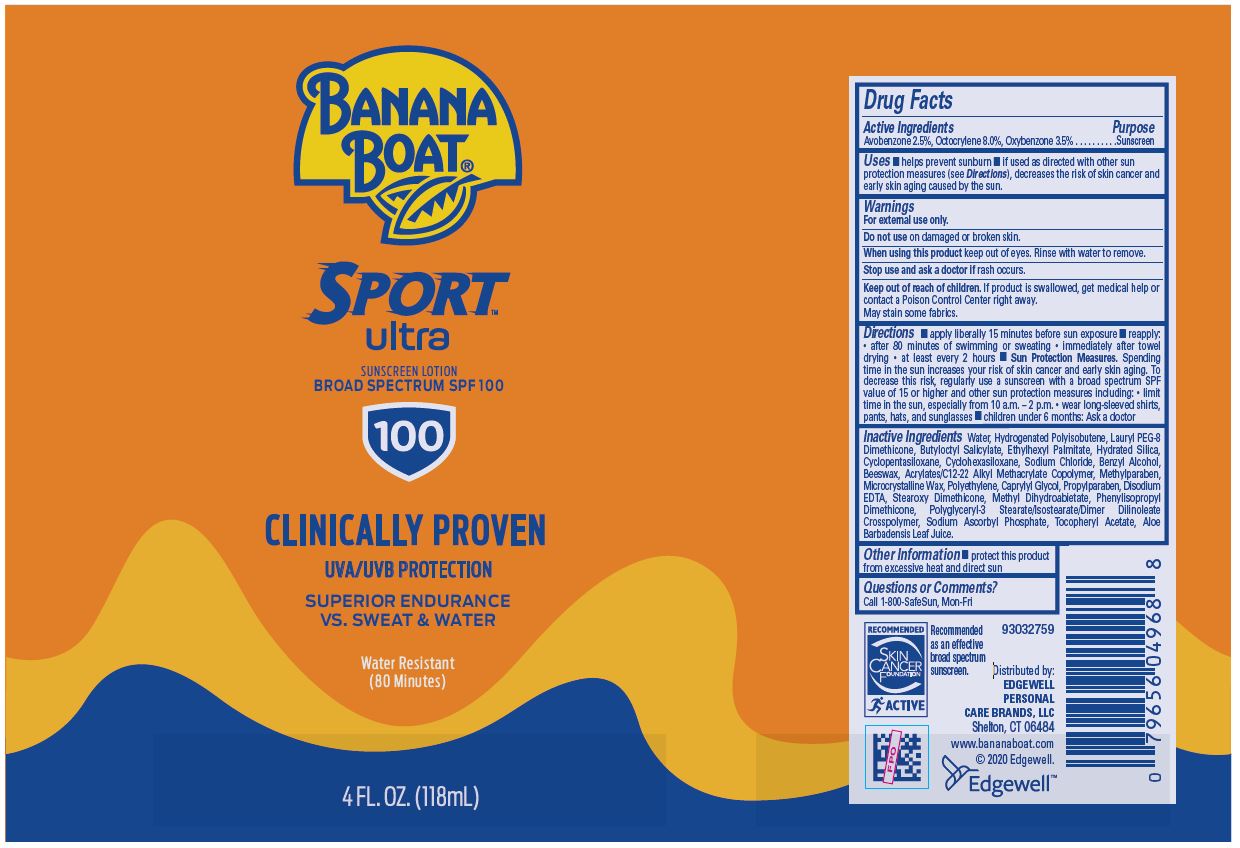 DRUG LABEL: Banana Boat
NDC: 63354-911 | Form: LOTION
Manufacturer: Edgewell Personal Care Brands LLC
Category: otc | Type: HUMAN OTC DRUG LABEL
Date: 20250817

ACTIVE INGREDIENTS: AVOBENZONE 2.5 g/100 g; OCTOCRYLENE 8 g/100 g; OXYBENZONE 3.5 g/100 g
INACTIVE INGREDIENTS: CAPRYLYL GLYCOL; EDETATE DISODIUM; SODIUM ASCORBYL PHOSPHATE; BENZYL ALCOHOL; METHYLPARABEN; WATER; HYDROGENATED METHYL ABIETATE; ALOE VERA LEAF; BUTYLOCTYL SALICYLATE; ETHYLHEXYL PALMITATE; HYDRATED SILICA; CYCLOMETHICONE 5; CYCLOMETHICONE 6; SODIUM CHLORIDE; YELLOW WAX; MICROCRYSTALLINE WAX; HIGH DENSITY POLYETHYLENE

Active Ingredients

Avobenzone 2.5%, Octocrylene 8.0%, Oxybenzone 3.5%

Purpose

Sunscreen

Uses

• helps prevent sunburn • if used as directed with other sun protection measures (see Directions), decreases the risk of skin cancer and early skin aging caused by the sun.

Warnings

For external use only.

May stain some fabrics.

Do not use

on damaged or broken skin.

When using this product

keep out of eyes. Rinse with water to remove.

Stop use and ask a doctor

if rash occurs.

Keep out of reach of children.

If product is swallowed, get medical help or contact a Poison Control Center right away.

Directions

• apply liberally 15 minutes before sun exposure. • reapply: • after 80 minutes of swimming or sweating, • immediately after towel drying, • at least every 2 hours. Sun Protection Measures. Spending time in the sun increases your risk of skin cancer and early skin aging. To decrease this risk, regulrly use a sunscreen with a broad spectrum SPF of 15 or higher and other sun protection measures including: • limit time in the sun, especially from 10 a.m.-2 p.m., • wear long-sleeve shirts, pants, hats, and sunglasses • children under 6 months: Ask a doctor

Inactive ingredients

Water, Hydrogenated Polyisobutene, Lauryl PEG-8 Dimethicone, Butyloctyl Salicylate, Ethylhexyl Palmitate, Hydrated Silica, Cyclopentasiloxane, Cyclohexasiloxane, Sodium Chloride, Benzyl Alcohol, Beeswax, Acrylates/C12-22 Alkyl Methacrylate Copolymer, Methylparaben, Microcrystalline Wax, Polyethylene, Caprylyl Glycol, Propylparaben, Disodium EDTA, Stearoxy Dimethicone, Methyl Dihydroabietate, Phenylisopropyl Dimethicone, Polyglyceryl-3 Stearate/Isostearate/Dimer Dilinoleate Crosspolymer, Sodium Ascorbyl Phosphate, Tocopheryl Acetate, Aloe Barbadensis Leaf Juice.

Other Information

• protect this product from excessive heat and direct sun

Questions or Comments?

Call 1 800 SafeSun, Mon-Fri

Primary Display Panel

BANANA
BOAT®
SPORT
ultra
SUNSCREEN LOTION
BROAD SPECTRUM SPF 100
100
CLINICALLY PROVEN
UVA/UVB PROTECTIO
SUPERIOR ENDURANCE
VS. SWEAT & WATER
Water Resistant
(80 Minutes)
4 FL. OZ. (118mL)